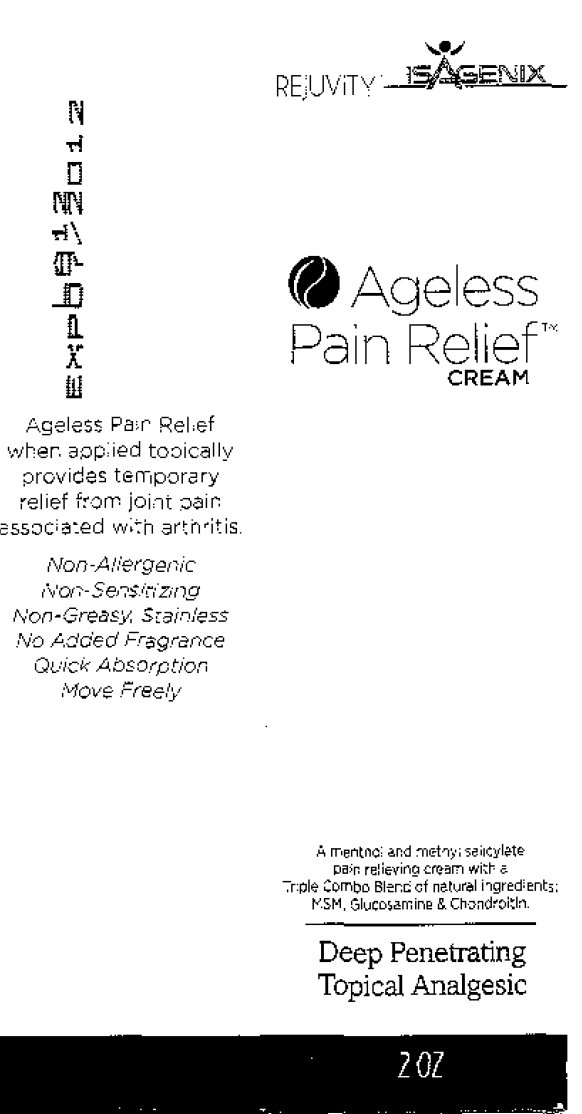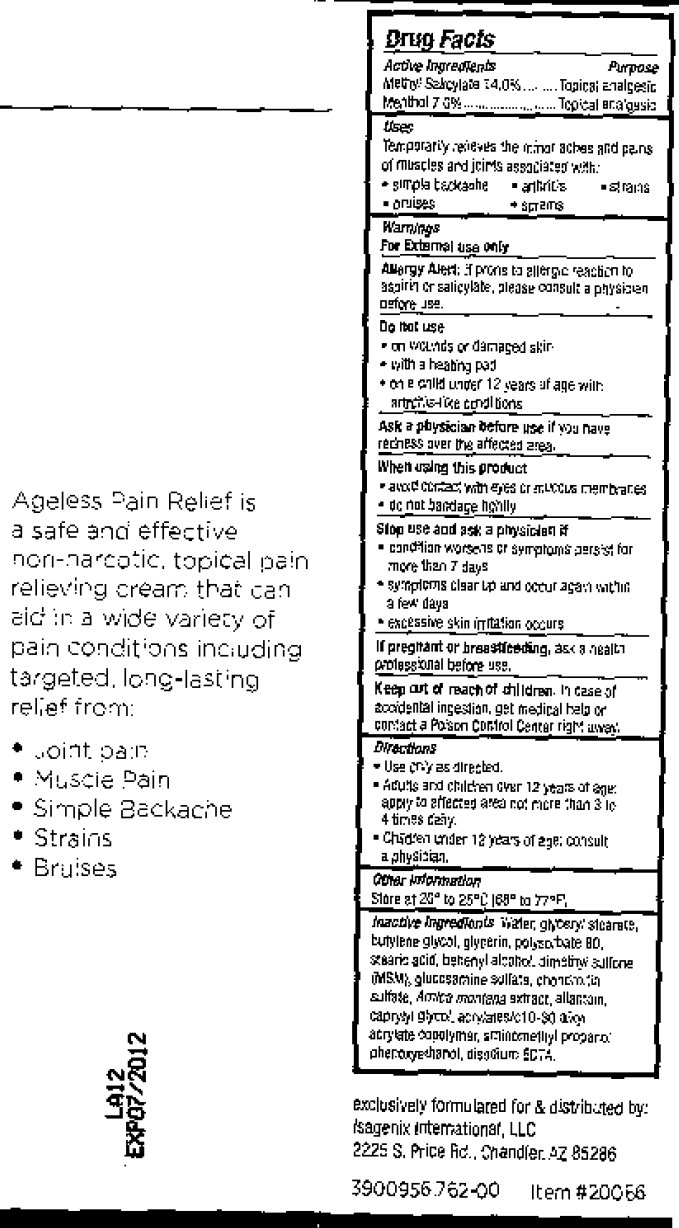 DRUG LABEL: Ageless Pain Relief
NDC: 76187-762 | Form: CREAM
Manufacturer: Isagenix International, LLC
Category: otc | Type: HUMAN OTC DRUG LABEL
Date: 20231212

ACTIVE INGREDIENTS: METHYL SALICYLATE 140 mg/1 mL; MENTHOL 70 mg/1 mL
INACTIVE INGREDIENTS: PHENOXYETHANOL; EDETATE DISODIUM; WATER; GLYCERYL MONOSTEARATE; BUTYLENE GLYCOL; GLYCERIN; POLYSORBATE 80; STEARIC ACID; CHONDROITIN SULFATE (BOVINE); CAPRYLYL GLYCOL

Ageless Pain Relief Cream

ACTIVE INGREDIENT

Active Ingredients Methyl Salicylate 14.0%.............. Menthol 7.0%.............................

Purpose

Topical Analgesic

INDICATIONS AND USAGE

Uses Temporarily receives the minor aches and pains of muscles and joints associated with: - simple backache - anthrics - strains - oruises - screms

Warnings For external use only

Allergy Alert: If proris to allergic reaction to aspirin or salicylate, please consult a physician before use.

Do not use - on wounds or damaged skin - with a heating pad - on a child under 12 years of age with artricithtice conditions.

ASK DOCTOR/PHARMACIST

Ask a physician before use if you have rechess over the affected area.

When using this product - avoid contact with eyes cremuccus remembranes - do not bandage highly.

Stop use and ask a physician if - condition worsons of symptoms persist for more than 7 days - symptons clear up and occur again within a few days - excessive skin irritation occurs.

PREGNANCY OR BREAST FEEDING

If pregnant or breastfeeding, ask a health professional before use.

Keep out of reach of children. In case of accidental ingestion, get medical help or contact a Poison Control Center right away.

DOSAGE AND ADMINISTRATION

Directions - Use only as directed - Adults and children over 12 years of ager. apply to affected area not more than 3 to 4 times daily. - children under 12 years of age: consult a physician.

Other information Store at 20 degree to 25 degree Centigrade (68 degree to 77 degree F).

INACTIVE INGREDIENT

Inactive Ingredients: Water, Glyceryl Stearate, Butylene Glycol, Glycerin, Polysorbate 80, Stearic Acid, Bezenyl Alcohol, dimethyl bullione (MSW), gluccsarmine silica, chondroitin sulfate, amica montena extract, allantain, caprylyl glycol, acrylated 10-80 alvon acrylate copolymer, smincernellyl proprol, phenoxyethanol, disodium EDTA.

DESCRIPTION

Ageless Pain Relief when applied topically provides temporary relef from joint pain associated with arthrits. Non-Allergenic Non-Sensinizing Non-Greasy, Stainless No Added Fragrance Quick Absorption Move Freely Ageless Pain Relief is a safe and effective non-narcotic topical pain relieving cream that can add in a wide variety of pain conditions including targeted. long-lastings relief from: - Joint pain - Muscle Pain - Simple Backache - Strains - Bruises exclusively formulated for and distributed by: Isagenix International, LLC 2225 S. Price Rd., Chandier.AZ 85286 3900956762-00 Item #20056

PACKAGE LABEL

REJUVITY ISAGENIX Ageless Pain Relief CREAM A Menthol and methyl salicylate pain relieving cream with a Triple Combo Blend of natural ingredients: MSM, Glucosaming and Chondroitin. Deep Penetrating Topical Analgesic 2 OZ

PACKAGE LABEL

LA12 EXP07/2012 exclusively formulated for and distributed by: Isagenix International, LLC 2225 S. Price Rd., Chandier.AZ 85286 3900956762-00 Item #20056